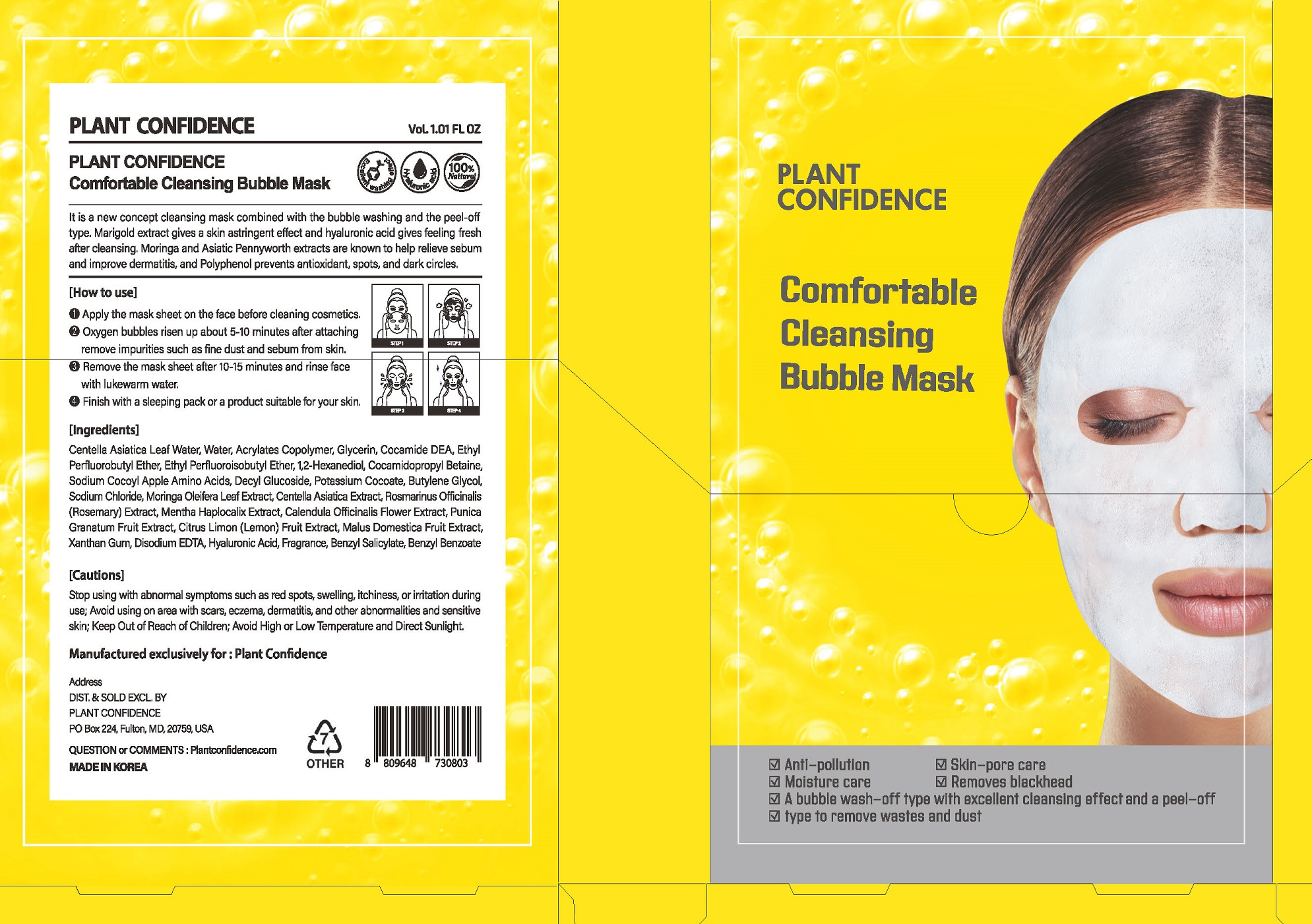 DRUG LABEL: PLANT CONFLDENCE Comfortable Cleansing Bubble Mask
NDC: 71484-0011 | Form: LIQUID
Manufacturer: Ddoruroo Co., Ltd.
Category: otc | Type: HUMAN OTC DRUG LABEL
Date: 20210129

ACTIVE INGREDIENTS: MORINGA OLEIFERA LEAF 0.3 g/100 mL
INACTIVE INGREDIENTS: WATER; BUTYLENE GLYCOL

Drug Facts

ACTIVE INGREDIENT

Moringa Oleifera Leaf Extract

INACTIVE INGREDIENT

Centella Asiatica Leaf Water
Water
Acrylates Copolymer
Glycerin
Cocamide DEA
Ethyl Perfluorobutyl Ether
Ethyl Perfluoroisobutyl Ether
1,2-Hexanediol
Cocamidopropyl Betaine
Sodium Cocoyl Apple Amino Acids
Decyl Glucoside
Potassium Cocoate
Butylene Glycol
Sodium Chloride
Centella Asiatica Extract
Rosmarinus Officinalis (Rosemary) Extract
Mentha Haplocalix Extract
Calendula Officinalis Flower Extract
Punica Granatum Fruit Extract
Citrus Limon (Lemon) Fruit Extract
Malus Domestica Fruit Extract
Xanthan Gum
Disodium EDTA
Hyaluronic Acid
Fragrance
Benzyl Salicylate
Benzyl Benzoate

PURPOSE

anti pollution, skin pora cara, moisture care, etc

KEEP OUT OF REACH OF THE CHILDREN

INDICATIONS AND USAGE

apply the mask sheet on the fact before cleaning cosmetics

remove he mask sheet after 10-15 minutes and rinse face with lukewarm water

WARNINGS

1. Do not use in the following cases (Eczema and scalp wounds)
2.Side Effects
1)Due to the use of this druf if rash, irritation, itching and symptopms of hypersnesitivity occur dicontinue use and consult your phamacisr or doctor
3.General Precautions
1)If in contact with the eyes, wash out thoroughty with water If the symptoms are servere, seek medical advice immediately
2)This product is for exeternal use only. Do not use for internal use
4.Storage and handling precautions
1)If possible, avoid direct sunlight and store in cool and area of low humidity
2)In order to maintain the quality of the product and avoid misuse
3)Avoid placing the product near fire and store out in reach of children

DOSAGE AND ADMINISTRATION

for external use only